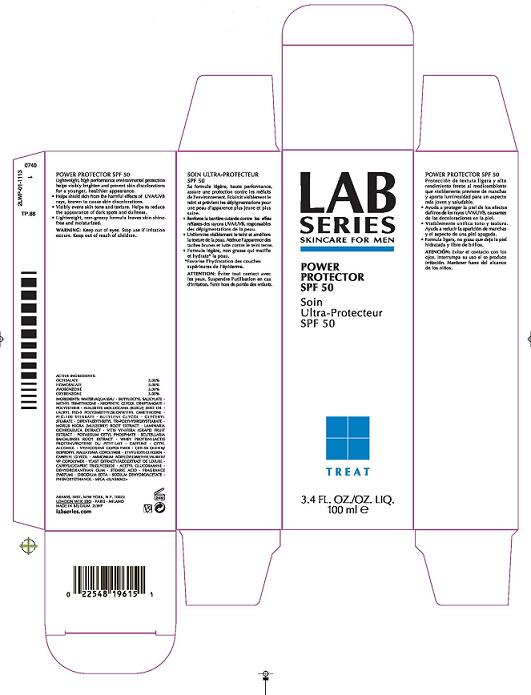 DRUG LABEL: ARAMIS LAB SERIES POWER PROTECTOR
NDC: 42472-720 | Form: LOTION
Manufacturer: ARAMIS INC
Category: otc | Type: HUMAN OTC DRUG LABEL
Date: 20100406

ACTIVE INGREDIENTS: OCTISALATE 5.0 mL/100 mL; HOMOSALATE 5.00 mL/100 mL; AVOBENZONE 3.00 1/100 mL; OXYBENZONE 3.00 mL/100 mL

ACTIVE INGREDIENT

ACTIVE INGREDIENTS: OCTISALATE 5.00% [] HOMOSALATE 5.00% [] AVOBENZONE 3.00% [] OXYBENZONE 3.00%

WARNINGS

WARNING: KEEP OUT OF EYES. STOP USE IF IRRITATION OCCURS. KEEP OUT OF REACH OF CHILDREN.

PACKAGE LABEL

PRINCIPAL DISPLAY PANEL:

ARAMIS

LAB SERIES
POWER PROTECTOR SPF 50
SKIN CARE FOR MEN

3.4 FL OZ/ 100 ML

ARAMIS INC.
NEW YORK, NY 10022